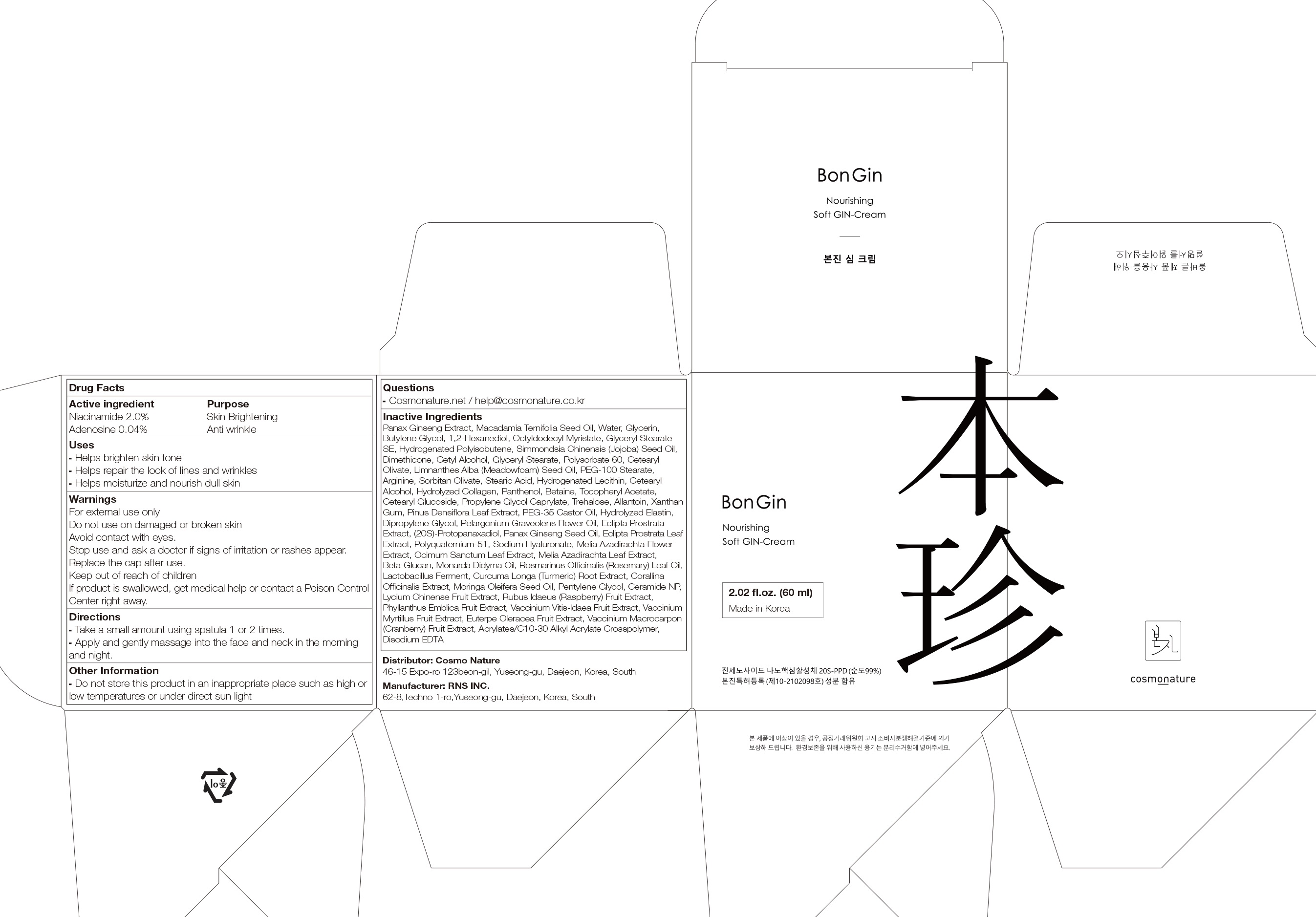 DRUG LABEL: BonGin Rebalancing GIN
NDC: 82492-030 | Form: CREAM
Manufacturer: Cosmo Nature
Category: otc | Type: HUMAN OTC DRUG LABEL
Date: 20231213

ACTIVE INGREDIENTS: Niacinamide 2.0 g/100 mL; Adenosine 0.04 g/100 mL
INACTIVE INGREDIENTS: MACADAMIA OIL; Water; Glycerin; Butylene Glycol; 1,2-Hexanediol

ACTIVE INGREDIENTS

Niacinamide 2.0%
Adenosine 0.04%

INACTIVE INGREDIENTS

Panax Ginseng Extract, Macadamia Ternifolia Seed Oil, Water, Glycerin, Butylene Glycol, 1,2-Hexanediol, Octyldodecyl Myristate, Glyceryl Stearate SE, Hydrogenated Polyisobutene, Simmondsia Chinensis (Jojoba) Seed Oil, Dimethicone, Cetyl Alcohol, Glyceryl Stearate, Polysorbate 60, Cetearyl Olivate, Limnanthes Alba (Meadowfoam) Seed Oil, PEG-100 Stearate, Arginine, Sorbitan Olivate, Stearic Acid, Hydrogenated Lecithin, Cetearyl Alcohol, Hydrolyzed Collagen, Panthenol, Betaine, Tocopheryl Acetate, Cetearyl Glucoside, Propylene Glycol Caprylate, Trehalose, Allantoin, Xanthan Gum, Pinus Densiflora Leaf Extract, PEG-35 Castor Oil, Hydrolyzed Elastin, Dipropylene Glycol, Pelargonium Graveolens Flower Oil, Eclipta Prostrata Extract, (20S)-Protopanaxadiol, Panax Ginseng Seed Oil, Eclipta Prostrata Leaf Extract, Polyquaternium-51, Sodium Hyaluronate, Melia Azadirachta Flower Extract, Ocimum Sanctum Leaf Extract, Melia Azadirachta Leaf Extract, Beta-Glucan, Monarda Didyma Oil, Rosmarinus Officinalis (Rosemary) Leaf Oil, Lactobacillus Ferment, Curcuma Longa (Turmeric) Root Extract, Corallina Officinalis Extract, Moringa Oleifera Seed Oil, Pentylene Glycol, Ceramide NP, Lycium Chinense Fruit Extract, Rubus Idaeus (Raspberry) Fruit Extract, Phyllanthus Emblica Fruit Extract, Vaccinium Vitis-Idaea Fruit Extract, Vaccinium Myrtillus Fruit Extract, Euterpe Oleracea Fruit Extract, Vaccinium Macrocarpon (Cranberry) Fruit Extract, Acrylates/C10-30 Alkyl Acrylate Crosspolymer, Disodium EDTA

PURPOSE

Skin Brightening
Anti wrinkle

WARNINGS

For external use only
Do not use on damaged or broken skin
Avoid contact with eyes.
Stop use and ask a doctor if signs of irritation or rashes appear.
Replace the cap after use.
Keep out of reach of children
If product is swallowed, get medical help or contact a Poison Control Center right away.

KEEP OUT OF REACH OF CHILDREN

Uses

■ Helps brighten skin tone
■ Helps repair the look of lines and wrinkles
■ Helps moisturize and nourish dull skin

Directions

■Take a small amount using spatula 1 or 2 times.
■ Apply and gently massage into the face and neck in the morning and night.

Other Information

■ Do not store this product in an inappropriate place such as high or low temperatures or under direct sun light

Questions

■ Cosmonature.net / help@cosmonature.co.kr